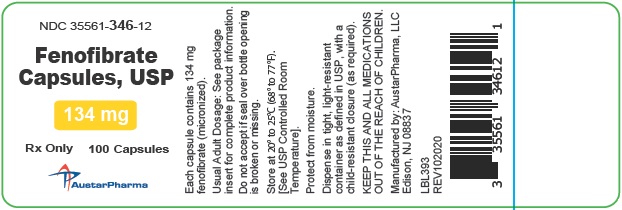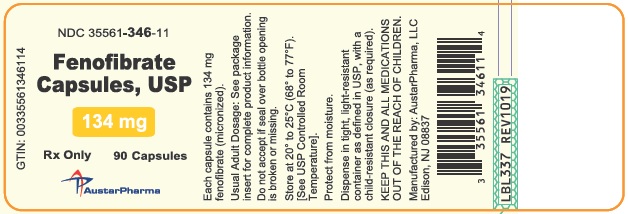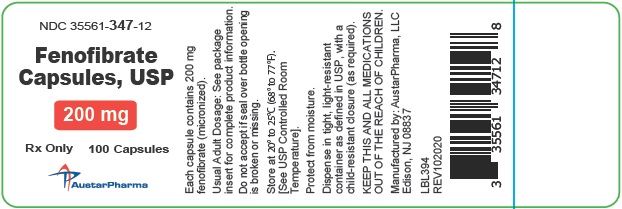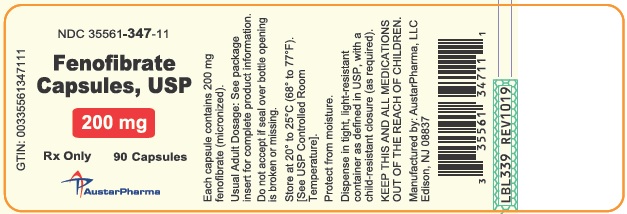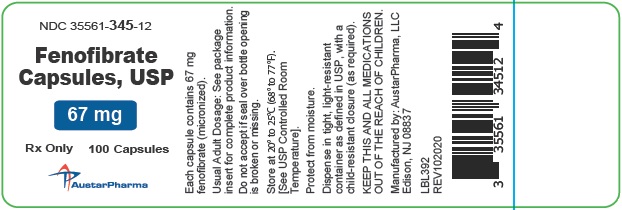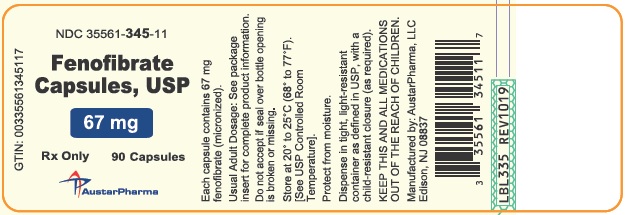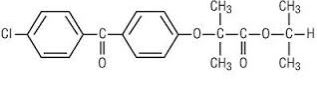 DRUG LABEL: Fenofibrate
NDC: 35561-346 | Form: CAPSULE
Manufacturer: Bostal LLC
Category: prescription | Type: HUMAN PRESCRIPTION DRUG LABEL
Date: 20260204

ACTIVE INGREDIENTS: FENOFIBRATE 134 mg/1 1

Fenofibrate Capsules, USP

Rx only

DESCRIPTION

Fenofibrate capsules, USP (micronized) are a lipid regulating agent available as capsules for oral administration. The chemical name for fenofibrate is 2-[4-(4- chlorobenzoyl) phenoxy]-2-methyl-propanoic acid, 1-methylethyl ester with the following structural formula:

The empirical formula is C20H21O4Cl and the molecular weight is 360.83; fenofibrate is insoluble in water. The melting point is 79° to 82°C. Fenofibrate is a white solid which is stable under ordinary conditions.

Each 67 mg fenofibrate capsule, USP contains the following inactive ingredients: sodium lauryl sulfate, croscarmellose sodium, pregelatinized starch, microcrystalline cellulose, colloidal silicon dioxide, sodium stearyl fumarate, titanium dioxide and gelatin. The capsule shell imprinting ink contains the following inactive ingredients: shellac, black iron oxide and potassium hydroxide.

Each 134 mg fenofibrate capsule, USP contains the following inactive ingredients: sodium lauryl sulfate, croscarmellose sodium, pregelatinized starch, microcrystalline cellulose, colloidal silicon dioxide, sodium stearyl fumarate, titanium dioxide, FD&C Yellow 6, D&C Yellow 10 and gelatin. The capsule shell imprinting ink contains the following inactive ingredients: shellac, black iron oxide and potassium hydroxide.

Each 200 mg fenofibrate capsule, USP contains the following inactive ingredients: sodium lauryl sulfate, croscarmellose sodium, pregelatinized starch, microcrystalline cellulose, colloidal silicon dioxide, sodium stearyl fumarate, titanium dioxide, FD&C Yellow 6, D&C Yellow 10 and gelatin. The capsule shell imprinting ink contains the following inactive ingredients: shellac, black iron oxide and potassium hydroxide.

CLINICAL PHARMACOLOGY

A variety of clinical studies have demonstrated that elevated levels of total cholesterol (total-C), low density lipoprotein cholesterol (LDL-C), and apolipoprotein B (apo B), an LDL membrane complex, are associated with human atherosclerosis. Similarly, decreased levels of high density lipoprotein cholesterol (HDL-C) and its transport complex, apolipoprotein A (apo AI and apo AII) are associated with the development of atherosclerosis. Epidemiologic investigations have established that cardiovascular morbidity and mortality vary directly with the level of total-C, LDL-C, and triglycerides, and inversely with the level of HDL-C. The independent effect of raising HDL-C or lowering triglycerides (TG) on the risk of cardiovascular morbidity and mortality has not been determined.

Fenofibric acid, the active metabolite of fenofibrate, produces reductions in total cholesterol, LDL cholesterol, apolipoprotein B, total triglycerides and triglyceride rich lipoprotein (VLDL) in treated patients. In addition, treatment with fenofibrate results in increases in high density lipoprotein (HDL) and apoproteins apo AI and apo AII.

The effects of fenofibric acid seen in clinical practice have been explained in vivo in transgenic mice and in vitro in human hepatocyte cultures by the activation of peroxisome proliferator activated receptor α (PPARα). Through this mechanism, fenofibrate increases lipolysis and elimination of triglyceride-rich particles from plasma by activating lipoprotein lipase and reducing production of apoproteins C-III (an inhibitor of lipoprotein lipase activity). The resulting fall in triglycerides produces an alteration in the size and composition of LDL from small, dense particles (which are thought to be atherogenic due to their susceptibility to oxidation), to large buoyant particles. These larger particles have a greater affinity for cholesterol receptors and are catabolized rapidly. Activation of PPARα also induces an increase in the synthesis of apoproteins A-I, A-II and HDL-cholesterol.

Fenofibrate also reduces serum uric acid levels in hyperuricemic and normal individuals by increasing the urinary excretion of uric acid.

INDICATIONS AND USAGE

Treatment of Hypercholesterolemia

Fenofibrate capsules, USP are indicated as adjunctive therapy to diet for the reduction of LDL-C, Total-C, Triglycerides and apo B in adult patients with primary hypercholesterolemia or mixed dyslipidemia (Fredrickson Types IIa and IIb). Lipid altering agents should be used in addition to a diet restricted in saturated fat and cholesterol when response to diet and non-pharmacological interventions alone has been inadequate (see National Cholesterol Education Program [NCEP] Treatment Guidelines, below).

Treatment of Hypertriglyceridemia

Fenofibrate capsules, USP are also indicated as adjunctive therapy to diet for treatment of adult patients with hypertriglyceridemia (Fredrickson Types IV and V hyperlipidemia). Improving glycemic control in diabetic patients showing fasting chylomicronemia will usually reduce fasting triglycerides and eliminate chylomicronemia thereby obviating the need for pharmacologic intervention.

Markedly elevated levels of serum triglycerides (e.g. > 2,000 mg/dL) may increase the risk of developing pancreatitis. The effect of fenofibrate therapy on reducing this risk has not been adequately studied.

Drug therapy is not indicated for patients with Type I hyperlipoproteinemia, who have elevations of chylomicrons and plasma triglycerides, but who have normal levels of very low density lipoprotein (VLDL). Inspection of plasma refrigerated for 14 hours is helpful in distinguishing Types I, IV and V hyperlipoproteinemia2.

The initial treatment for dyslipidemia is dietary therapy specific for the type of lipoprotein abnormality. Excess body weight and excess alcoholic intake may be important factors in hypertriglyceridemia and should be addressed prior to any drug therapy. Physical exercise can be an important ancillary measure. Diseases contributory to hyperlipidemia, such as hypothyroidism or diabetes mellitus should be looked for and adequately treated. Estrogen therapy, like thiazide diuretics and beta-blockers, is sometimes associated with massive rises in plasma triglycerides, especially in subjects with familial hypertriglyceridemia. In such cases, discontinuation of the specific etiologic agent may obviate the need for specific drug therapy of hypertriglyceridemia.

The use of drugs should be considered only when reasonable attempts have been made to obtain satisfactory results with non-drug methods. If the decision is made to use drugs, the patient should be instructed that this does not reduce the importance of adhering to diet (See WARNINGS and PRECAUTIONS).

Fredrickson Classification of Hyperlipoproteinemias
Type | Lipoprotein Elevated | Lipid Elevation
Type | Lipoprotein Elevated | Major | Minor
I (rare) | Chylomicrons | TG | ↑↔C
IIa | LDL | C | —
IIb | LDL, VLDL | C | TG
III (rare) | IDL | C, TG | —
IV | VLDL | TG | ↑↔C
V (rare) | Chylomicrons, VLDL | TG | ↑↔
C = cholesterol
TG = triglycerides
LDL = low density lipoprotein
VLDL = very low density lipoprotein
IDL = intermediate density lipoprotein

The NCEP Treatment Guidelines
Definite Athlerosclerotic Disease* | Two or More Other Risk Factors† | LDL-Cholesterol mg/dL (mmol/L)
Definite Athlerosclerotic Disease* | Two or More Other Risk Factors† | Initiation Level | Goal
No | No | ≥ 190 (≥ 4.9) | < 160 (< 4.1)
No | Yes | ≥ 160 (≥ 4.1) | < 130 (< 3.4)
Yes | Yes or No | ≥ 130‡ (≥ 3.4) | < 100 (< 2.6)

CONTRAINDICATIONS

Fenofibrate capsules are contraindicated in patients who exhibit hypersensitivity to fenofibrate.

Fenofibrate capsules are contraindicated in patients with hepatic or severe renal dysfunction, including primary biliary cirrhosis, and patients with unexplained persistent liver function abnormality.

Fenofibrate capsules are contraindicated in patients with preexisting gallbladder disease (see WARNINGS).

WARNINGS

Liver Function

Fenofibrate capsules at doses equivalent to 134 mg to 200 mg fenofibrate per day has been associated with increases in serum transaminases [AST (SGOT) or ALT (SGPT)]. In a pooled analysis of 10 placebo-controlled trials, increases to > 3 times the upper limit of normal occurred in 5.3% of patients taking fenofibrate versus 1.1% of patients treated with placebo.

When transaminase determinations were followed either after discontinuation of treatment or during continued treatment, a return to normal limits was usually observed. The incidence of increases in transaminase related to fenofibrate therapy appear to be dose related. In an 8 week dose-ranging study, the incidence of ALT or AST elevations to at least three times the upper limit of normal was 13% in patients receiving dosages equivalent to 134 mg to 200 mg fenofibrate per day and was 0% in those receiving dosages equivalent to 34 mg or 67 mg of fenofibrate per day or placebo. Hepatocellular, chronic active and cholestatic hepatitis associated with fenofibrate therapy have been reported after exposures of weeks to several years. In extremely rare cases, cirrhosis has been reported in association with chronic active hepatitis.

Regular periodic monitoring of liver function, including serum ALT (SGPT) should be performed for the duration of therapy with fenofibrate, and therapy discontinued if enzyme levels persist above three times the normal limit.

Cholelithiasis

Fenofibrate, like clofibrate and gemfibrozil, may increase cholesterol excretion into the bile, leading to cholelithiasis. If cholelithiasis is suspected, gallbladder studies are indicated. Fenofibrate therapy should be discontinued if gallstones are found.

Concomitant Oral Anticoagulants

Caution should be exercised when anticoagulants are given in conjunction with fenofibrate because of the potentiation of coumarin-type anticoagulants in prolonging the prothrombin time/INR. The dosage of the anticoagulant should be reduced to maintain the prothrombin time/lNR at the desired level to prevent bleeding complications. Frequent prothrombin time/INR determinations are advisable until it has been definitely determined that the prothrombin time/INR has stabilized.

Concomitant HMG-CoA Reductase Inhibitors

The combined use of fenofibrate and HMG-CoA reductase inhibitors should be avoided unless the benefit of further alterations in lipid levels is likely to outweigh the increased risk of this drug combination.

Concomitant administration of fenofibrate (equivalent to fenofibrate 200 mg) and pravastatin (40 mg) once daily for 10 days increased the mean Cmax and AUC values for pravastatin by 36% (range from 69% decrease to 321% increase) and 28% (range from 54% decrease to 128% increase), respectively, and for 3α-hydroxy-iso-pravastatin by 55% (range from 32% decrease to 314% increase) and 39% (range from 24% decrease to 261% increase), respectively. (See also CLINICAL PHARMACOLOGY, Drug-drug interactions.)

The combined use of fibric acid derivatives and HMG-CoA reductase inhibitors has been associated, in the absences of a marked pharmacokinetic interaction, in numerous case reports, with rhabdomyolysis, markedly elevated creatine kinase (CK) levels and myoglobinuria, leading in a high proportion of cases to acute renal failure.

The use of fibrates alone, including fenofibrate capsules may occasionally be associated with myositis, myopathy, or rhabdomyolysis. Patients receiving fenofibrate and complaining of muscle pain, tenderness, or weakness should have prompt medical evaluation for myopathy, including serum creatine kinase level determination. If myopathy/myositis is suspected or diagnosed, fenofibrate therapy should be stopped.

Mortality

The effect of fenofibrate on coronary heart disease morbidity and mortality and non-cardiovascular mortality has not been established.

Other Considerations

The Fenofibrate Intervention and Event Lowering in Diabetes (FIELD) study was a 5 year randomized, placebo-controlled study of 9,795 patients with type 2 diabetes mellitus treated with fenofibrate.

Fenofibrate demonstrated a non-significant 11% relative reduction in the primary outcome of coronary heart disease events (hazard ratio [HR] 0.89, 95% CI 0.75-1.05, p=0.16) and a significant 11% reduction in the secondary outcome of total cardiovascular disease events (HR 0.89 [0.80 to 0.99], p=0.04). There was a non-significant 11% (HR 1.11 [0.95, 1.29], p=0.18) and 19% (HR 1.19 [0.90, 1.57], p=0.22) increase in total and coronary heart disease mortality, respectively, with fenofibrate as compared to placebo.

In the Coronary Drug Project, a large study of post myocardial infarction of patients treated for 5 years with clofibrate, there was no difference in mortality seen between the clofibrate group and the placebo group. There was however, a difference in the rate of cholelithiasis and cholecystitis requiring surgery between the two groups (3% vs. 1.8%).

Because of chemical, pharmacological, and clinical similarities between fenofibrate, clofibrate, and gemfibrozil, the adverse findings in 4 large randomized, placebo-controlled clinical studies with these other fibrate drugs may also apply to fenofibrate.

In a study conducted by the World Health Organization (WHO), 5,000 subjects without known coronary artery disease were treated with placebo or clofibrate for 5 years and followed for an additional one year. There was a statistically significant, higher age-adjusted all-cause mortality in the clofibrate group compared with the placebo group (5.70% vs. 3.96%, p=<0.01). Excess mortality was due to a 33% increase in non-cardiovascular causes, including malignancy, post-cholecystectomy complications, and pancreatitis. This appeared to confirm the higher risk of gallbladder disease seen in clofibrate-treated patients studied in the Coronary Drug Project.

The Helsinki Heart Study was a large (n=4,081) study of middle-aged men without a history of coronary artery disease. Subjects received either placebo or gemfibrozil for 5 years, with a 3.5 year open extension afterward. Total mortality was numerically higher in the gemfibrozil randomization group but did not achieve statistical significance (p=0.19, 95% confidence interval for relative risk G:P=0.91 to 1.64). Although cancer deaths trended higher in the gemfibrozil group (p=0.11), cancers (excluding basal cell carcinoma) were diagnosed with equal frequency in both study groups. Due to the limited size of the study, the relative risk of death from any cause was not shown to be different than that seen in the 9 year follow-up data from World Health Organization study (RR=1.29). Similarly, the numerical excess of gallbladder surgeries in the gemfibrozil group did not differ statistically from that observed in the WHO study.

A secondary prevention component of the Helsinki Heart Study enrolled middle aged men excluded from the primary prevention study because of known or suspected coronary heart disease. Subjects received gemfibrozil or placebo for 5 years. Although cardiac deaths trended higher in the gemfibrozil group, this was not statistically significant (hazard ratio 2.2, 95% confidence interval: 0.94-5.05). The rate of gallbladder surgery was not statistically significant between study groups, but did trend higher in the gemfibrozil group, (1.9% vs. 0.3%, p=0.07).

There was a statistically significant difference in the number of appendectomies in the gemfibrozil group (6/311 vs. 0/317, p=0.029).

PRECAUTIONS

Initial Therapy

Laboratory studies should be done to ascertain that the lipid levels are consistently abnormal before instituting fenofibrate therapy. Every attempt should be made to control serum lipids with appropriate diet, exercise, weight loss in obese patients, and control of any medical problems such as diabetes mellitus and hypothyroidism that are contributing to the lipid abnormalities. Medications known to exacerbate hypertriglyceridemia (beta-blockers, thiazides, estrogens) should be discontinued or changed if possible prior to consideration of triglyceride-lowering drug therapy.

Continued Therapy

Periodic determination of serum lipids should be obtained during initial therapy in order to establish the lowest effective dose of fenofibrate capsules. Therapy should be withdrawn in patients who do not have an adequate response after two months of treatment with the maximum recommended dose of 200 mg per day.

Pancreatitis

Pancreatitis has been reported in patients taking fenofibrate, gemfibrozil, and clofibrate. This occurrence may represent a failure of efficacy in patients with severe hypertriglyceridemia, a direct drug effect, or a secondary phenomenon mediated through biliary tract stone or sludge formation with obstruction of the common bile duct.

Hypersensitivity Reactions

Acute Hypersensitivity: Anaphylaxis and angioedema have been reported postmarketing with fenofibrate. In some cases, reactions were life-threatening and required emergency treatment. If a patient develops signs or symptoms of an acute hypersensitivity reaction, advise them to seek immediate medical attention and discontinue fenofibrate.

Delayed Hypersensitivity: Severe cutaneous adverse drug reactions (SCAR), including Stevens-Johnson Syndrome, Toxic Epidermal Necrolysis, and Drug Reaction with Eosinophilia and Systemic Symptoms (DRESS), have been reported postmarketing, occurring days to weeks after initiation of fenofibrate. The cases of DRESS were associated with cutaneous reactions (such as rash or exfoliative dermatitis) and a combination of eosinophilia, fever, systemic organ involvement (renal, hepatic, or respiratory). Discontinue fenofibrate and treat patients appropriately if SCAR is suspected.

Hematologic Changes

Mild to moderate hemoglobin, hematocrit, and white blood cell decreases have been observed in patients following initiation of fenofibrate therapy. However, these levels stabilize during long-term administration. Extremely rare spontaneous reports of thrombocytopenia and agranulocytosis have been received during postmarketing surveillance outside of the U.S. Periodic blood counts are recommended during the first 12 months of fenofibrate administration.

Skeletal Muscle

The use of fibrates alone, including fenofibrate, may occasionally be associated with myopathy. Treatment with drugs of the fibrate class has been associated on rare occasions with rhabdomyolysis, usually in patients with impaired renal function. Myopathy should be considered in any patient with diffuse myalgias, muscle tenderness or weakness, and/or marked elevations of creatine phosphokinase levels.

Patients should be advised to report promptly unexplained muscle pain, tenderness or weakness, particularly if accompanied by malaise or fever. CPK levels should be assessed in patients reporting these symptoms, and fenofibrate therapy should be discontinued if markedly elevated CPK levels occur or myopathy is diagnosed.

Venothromboembolic Disease

In the FIELD trial, pulmonary embolus (PE) and deep vein thrombosis (DVT) were observed at higher rates in the fenofibrate- than the placebo-treated group. Of 9,795 patients enrolled in FIELD, there were 4,900 in the placebo group and 4,895 in the fenofibrate group. For DVT, there were 48 events (1%) in the placebo group and 67 (1%) in the fenofibrate group (p = 0.074); and for PE, there were 32 (0.7%) events in the placebo group and 53 (1%) in the fenofibrate group (p = 0.022).

In the Coronary Drug Project, a higher proportion of the clofibrate group experienced definite or suspected fatal or nonfatal pulmonary embolism or thrombophlebitis than the placebo group (5.2% vs. 3.3% at five years; p < 0.01).

Serum Creatinine

Elevations in serum creatinine have been reported in patients on fenofibrate. These elevations tend to return to baseline following discontinuation of fenofibrate. The clinical significance of these observations is unknown.

Drug Interactions

Oral Anticoagulants

CAUTION SHOULD BE EXERCISED WHEN COUMARIN ANTICOAGULANTS ARE GIVEN IN CONJUNCTION WITH FENOFIBRATE CAPSULES. THE DOSAGE OF THE ANTICOAGULANTS SHOULD BE REDUCED TO MAINTAIN THE PROTHROMBIN TIME/INR AT THE DESIRED LEVEL TO PREVENT BLEEDING COMPLICATIONS. FREQUENT PROTHROMBIN TIME/INR DETERMINATIONS ARE ADVISABLE UNTIL IT HAS BEEN DEFINITELY DETERMINED THAT THE PROTHROMBIN TIME/INR HAS STABILIZED.

HMG-CoA Reductase Inhibitors

The combined use of fenofibrate and HMG-CoA reductase inhibitors should be avoided unless the benefit of further alterations in lipid levels is likely to outweigh the increased risk of this drug combination (see WARNINGS).

Resins

Since bile acid sequestrants may bind other drugs given concurrently, patients should take fenofibrate capsules at least 1 hour before or 4 to 6 hours after a bile acid binding resin to avoid impeding its absorption.

Cyclosporine

Because cyclosporine can produce nephrotoxicity with decreases in creatinine clearance and rises in serum creatinine, and because renal excretion is the primary elimination route of fibrate drugs including fenofibrate, there is a risk that an interaction will lead to deterioration. The benefits and risks of using fenofibrate with immunosuppressants and other potentially nephrotoxic agents should be carefully considered, and the lowest effective dose employed.

Carcinogenesis, Mutagenesis, Impairment of Fertility

Two dietary carcinogenicity studies have been conducted in rats with fenofibrate. In the first 24 month study, rats were dosed with fenofibrate at 10, 45, and 200 mg/kg/day, approximately 0.3, 1, and 6 times the maximum recommended human dose (MRHD), based on body surface area comparisons (mg/m^2). At a dose of 200 mg/kg/day (at 6 times the MRHD), the incidence of liver carcinomas was significantly increased in both sexes. A statistically significant increase in pancreatic carcinomas was observed in males at 1 and 6 times the MRHD; an increase in pancreatic adenomas and benign testicular interstitial cell tumors was observed at 6 times the MRHD in males. In a second 24 month rat carcinogenicity study in a different strain of rats, doses of 10 and 60 mg/kg/day (0.3 and 2 times the MRHD) produced significant increases in the incidence of pancreatic acinar adenomas in both sexes and increases in testicular interstitial cell tumors in males at 2 times the MRHD.

A 117 week carcinogenicity study was conducted in rats comparing three drugs: fenofibrate 10 and 60 mg/kg/day (0.3 and 2 times the MRHD), clofibrate (400 mg/kg/day; 2 times the human dose), and gemfibrozil (250 mg/kg/day; 2 times the human dose, based on mg/m^2surface area). Fenofibrate increased pancreatic acinar adenomas in both sexes. Clofibrate increased hepatocellular carcinoma and pancreatic acinar adenomas in males and hepatic neoplastic nodules in females. Gemfibrozil increased hepatic neoplastic nodules in males and females, while all three drugs increased testicular interstitial cell tumors in males.

In a 21 month study in mice, fenofibrate 10, 45, and 200 mg/kg/day (approximately 0.2, 1, and 3 times the MRHD on the basis of mg/m^2 surface area) significantly increased the liver carcinomas in both sexes at 3 times the MRHD. In a second 18 month study at 10, 60, and 200 mg/kg/day, fenofibrate significantly increased the liver carcinomas in male mice and liver adenomas in female mice at 3 times the MRHD.

Electron microscopy studies have demonstrated peroxisomal proliferation following fenofibrate administration to the rat. An adequate study to test for peroxisome proliferation in humans has not been done, but changes in peroxisome morphology and numbers have been observed in humans after treatment with other members of the fibrate class when liver biopsies were compared before and after treatment in the same individual.

Fenofibrate has been demonstrated to be devoid of mutagenic potential in the following tests: Ames, mouse lymphoma, chromosomal aberration and unscheduled DNA synthesis in primary rat hepatocytes.

In fertility studies rats were given oral dietary doses of fenofibrate, males received 61 days prior to mating and females 15 days prior to mating through weaning which resulted in no adverse effect on fertility at doses up to 300 mg/kg/day (~ 10 times the MRHD, based on mg/m^2 surface area comparisons).

Pregnancy

Teratogenic Effects

Pregnancy category C

Safety in pregnant women has not been established. There are no adequate and well controlled studies of fenofibrate in pregnant women. Fenofibrate should be used during pregnancy only if the potential benefit justifies the potential risk to the fetus.

In female rats given oral dietary doses of 15, 75, and 300 mg/kg/day of fenofibrate from 15 days prior to mating through weaning, maternal toxicity was observed at 0.3 times the MRHD, based on body surface area comparisons; mg/m^2.

In pregnant rats given oral dietary doses of 14, 127, and 361 mg/kg/day from gestation day 6 to 15 during the period of organogenesis, adverse developmental findings were not observed at 14 mg/kg/day (less than 1 times the MRHD, based on body surface area comparisons; mg/m^2). At higher multiples of human doses evidence of maternal toxicity was observed.

In pregnant rabbits given oral gavage doses of 15, 150, and 300 mg/kg/day from gestation day 6 to 18 during the period of organogenesis and allowed to deliver, aborted litters were observed at 150 mg/kg/day (10 times the MRHD, based on body surface area comparisons: mg/m2). No developmental findings were observed at 15 mg/kg/day (at less than 1 times the MRHD, based on body surface area comparisons: mg/m^2).

In pregnant rats given oral dietary doses of 15, 75, and 300 mg/kg/day from gestation day 15 through lactation day 21 (weaning), maternal toxicity was observed at less than 1 times the MRHD, based on body surface area comparisons: mg/m^2.

Nursing Mothers

It is not known whether fenofibrate is excreted into milk. Because many drugs are excreted in human milk and because of the potential for serious adverse reactions in nursing infants from fenofibrate, a decision should be made whether to discontinue nursing or administration of fenofibrate taking into account the importance of the drug to the lactating woman.

Pediatric Use

Safety and efficacy in pediatric patients have not been established.

Geriatric Use

Fenofibric acid is known to be substantially excreted by the kidney, and the risk of adverse reactions to this drug may be greater in patients with impaired renal function. Fenofibric acid exposure is not influenced by age. However, elderly patients have a higher incidence of renal impairment, such that dose selection for the elderly should be made on the basis of renal function (see CLINICAL PHARMACOLOGY, Special Populations, Renal Insufficiency). Elderly patients with normal renal function should require no dose modifications.

ADVERSE REACTIONS

Photosensitivity reactions have occurred days to months after initiation; in some of these cases, patients reported a prior photosensitivity reaction to ketoprofen.

Clinical Trials Experience

Because clinical studies are conducted under widely varying conditions, adverse reaction rates observed in the clinical studies of a drug cannot be directly compared to rates in the clinical studies of another drug and may not reflect the rates observed in practice.

Adverse events reported by 2% or more of patients treated with fenofibrate (and greater than placebo) during the double-blind, placebo-controlled trials, regardless of causality, are listed in Table 3 below. Adverse events led to discontinuation of treatment in 5.0% of patients treated with fenofibrate and in 3.0% treated with placebo. Increases in liver function tests were the most frequent events, causing discontinuation of fenofibrate treatment in 1.6% of patients in double-blind trials.

Table 3. Adverse Reactions Reported by 2% or More of Patients Treated withFenofibrate and Greater than Placebo During the Double-Blind, Placebo-Controlled Trials

BODY SYSTEM Adverse Reaction | Fenofibrate* (N=439) | PLACEBO (N=365)
BODY AS A WHOLE
Abdominal Pain | 4.6% | 4.4%
Back Pain | 3.4% | 2.5%
Headache | 3.2% | 2.7%
DIGESTIVE
Abnormal Liver Function Tests | 7.5%† | 1.4%
Nausea | 2.3% | 1.9%
Constipation | 2.1% | 1.4%
METABOLIC AND NUTRITIONAL DISORDERS
Increased ALT | 3% | 1.6%
Increased CPK | 3% | 1.4%
Increased AST | 3.4%† | 0.5%
RESPIRATORY
Respiratory Disorder | 6.2% | 5.5%
Rhinitis | 2.3% | 1.1%

Post-Marketing Experience

The following adverse reactions have been identified during post-approval use of fenofibrate: myalgia, rhabdomyolysis, pancreatitis, acute renal failure, muscle spasm, hepatitis, cirrhosis, anemia, arthralgia, decreases in hemoglobin, decreases in hematocrit, white blood cell decreases and asthenia. Because these reactions are reported voluntarily from a population of uncertain size, it is not always possible to reliably estimate their frequency or establish a causal relationship to drug exposure.

OVERDOSAGE

There is no specific treatment for overdose with fenofibrate. General supportive care of the patient is indicated, including monitoring of vital signs and observation of clinical status, should an overdose occur. If indicated, elimination of unabsorbed drug should be achieved by emesis or gastric lavage; usual precautions should be observed to maintain the airway. Because fenofibrate is highly bound to plasma proteins, hemodialysis should not be considered.

DOSAGE AND ADMINISTRATION

Patients should be placed on an appropriate lipid-lowering diet before receiving fenofibrate capsules, and should continue this diet during treatment with fenofibrate capsules. Fenofibrate capsules should be given with meals, thereby optimizing the bioavailability of the medication.

For the treatment of adult patients with primary hypercholesterolemia or mixed hyperlipidemia, the initial dose of fenofibrate capsules is 200 mg per day.

For adult patients with hypertriglyceridemia, the initial dose is 67 mg to 200 mg per day.

Dosage should be individualized according to patient response, and should be adjusted if necessary following repeat lipid determinations at 4 to 8 week intervals. The maximum dose is 200 mg per day.

Treatment with fenofibrate capsules, should be initiated at a dose of 67 mg/day in patients having impaired renal function, and increased only after evaluation of the effects on renal function and lipid levels at this dose. In the elderly, the initial dose should likewise be limited to 67 mg/day.

Lipid levels should be monitored periodically and consideration should be given to reducing the dosage of fenofibrate capsules if lipid levels fall significantly below the targeted range.

HOW SUPPLIED

Fenofibrate capsules, USP (micronized) 67 mg are opaque white cap and body, hard gelatin capsules, printed in black ink “CL” and “22” on opposing cap and body portions of the capsule. They are supplied as follows:

NDC 35561-345-11 Bottles of 90 capsules

NDC 35561-345-12 Bottles of 100 capsules

Fenofibrate capsules, USP (micronized) 134 mg are opaque white cap and opaque yellow body, hard gelatin capsules, printed in black ink “CL” and “23” on opposing cap and body portions of the capsule. They are supplied as follows:

NDC 35561-346-11 Bottles of 90 capsules

NDC 35561-346-12 Bottles of 100 capsules

Fenofibrate capsules, USP (micronized) 200 mg are opaque yellow cap and body, hard gelatin capsules, printed in black ink “CL” and “24” on opposing cap and body portions of the capsule. They are supplied as follows:

NDC 35561-347-11 Bottles of 90 capsules

NDC 35561-347-12 Bottles of 100 capsules

STORAGE

Store at 20° to 25°C (68° to 77°F) [See USP Controlled Room Temperature]. Keep out of the reach of children. Protect from moisture. Dispense in tight, light-resistant container as defined in USP with a child-resistant closure (as required).

REFERENCES

1. GOLDBERG AC, et al. Fenofibrate for the Treatment of Type IV and V Hyperlipoproteinemias: A Double-Blind, Placebo-Controlled Multicenter US Study. Clinical Therapeutics, 11, pp. 69-83, 1989.
2. NIKKILA EA. Familial Lipoprotein Lipase Deficiency and Related Disorders of Chylomicron Metabolism. In Stanbury J.B., et al. (eds.): The Metabolic Basis of Inherited Disease, 5th edition, McGraw-Hill, 1983, Chap. 30, pp. 622-642.
3. BROWN WV, et al. Effects of Fenofibrate on Plasma Lipids: Double-Blind, Multicenter Study In Patients with Type IIA or IIB Hyperlipidemia. Arteriosclerosis. 6, pp. 670-678, 1986.

Manufactured by:

AustarPharma, LLC

Edison, NJ 08837 USA

Revised: 10/2020

LBL342

PRINCIPAL DISPLAY PANEL - 67 mg Capsule Bottle Label

NDC 35561- 345-11

Fenofibrate Capsules, USP

67 mg

Rx Only 90 Capsules

PRINCIPAL DISPLAY PANEL - 67 mg Capsule Bottle Label

NDC 35561- 345-12

Fenofibrate Capsules, USP

67 mg

Rx Only 100 Capsules

PRINCIPAL DISPLAY PANEL - 134 mg Capsule Bottle Label

NDC 35561- 346-11

Fenofibrate Capsules, USP

134 mg

Rx Only 90 Capsules

PRINCIPAL DISPLAY PANEL - 134 mg Capsule Bottle Label

NDC 35561- 346-12

Fenofibrate Capsules, USP

134 mg

Rx Only 100 Capsules

PRINCIPAL DISPLAY PANEL - 200 mg Capsule Bottle Label

NDC 35561- 347-11

Fenofibrate Capsules, USP

200 mg

Rx Only 90 Capsules

PRINCIPAL DISPLAY PANEL - 200 mg Capsule Bottle Label

NDC 35561- 347-12

Fenofibrate Capsules, USP

200 mg

Rx Only 100 Capsules